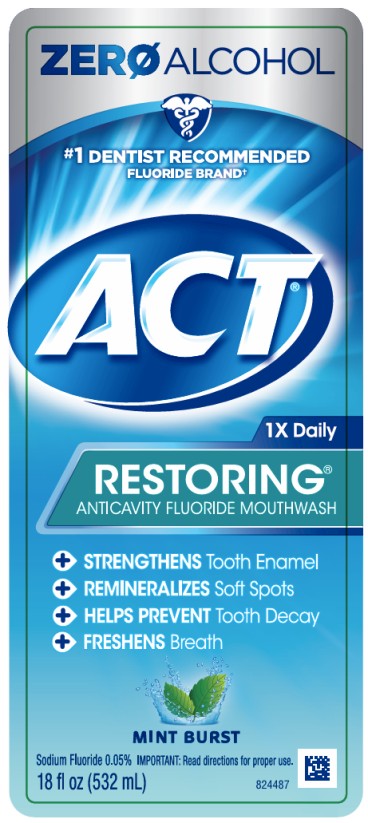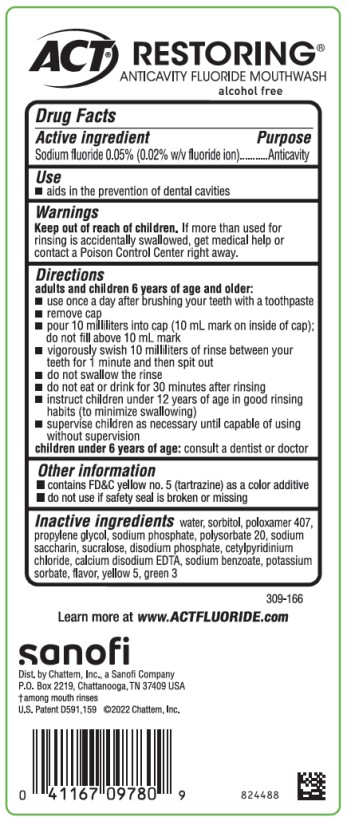 DRUG LABEL: ACT Restoring Anticavity Fluoride Mint Burst
NDC: 41167-0979 | Form: MOUTHWASH
Manufacturer: Chattem, Inc.
Category: otc | Type: HUMAN OTC DRUG LABEL
Date: 20250930

ACTIVE INGREDIENTS: SODIUM FLUORIDE 0.5 mg/1 mL
INACTIVE INGREDIENTS: WATER; SORBITOL; POLOXAMER 407; PROPYLENE GLYCOL; SODIUM PHOSPHATE; POLYSORBATE 20; SACCHARIN SODIUM; SUCRALOSE; SODIUM PHOSPHATE, DIBASIC, ANHYDROUS; CETYLPYRIDINIUM CHLORIDE; EDETATE CALCIUM DISODIUM ANHYDROUS; SODIUM BENZOATE; POTASSIUM SORBATE; FD&C YELLOW NO. 5; FD&C GREEN NO. 3

ACT Restoring Mint Burst

ACT® Restoring™ Mint Burst

Anticavity Fluoride Rinse

Drug Facts

Active ingredient

Sodium fluoride 0.05% (0.02% w/v fluoride ion)

Purpose

Anticavity

Use

- aids in the prevention of dental cavities

Warnings

Keep out of reach of children.

If more than used for rinsing is accidentally swallowed, get medical help or contact a Poison Control Center right away.

Directions

adults and children 6 years of age and older:

- use once a day after brushing your teeth with a toothpaste
- remove cap
- pour 10 milliliters into cap (10 mL mark on inside of cap); do not fill above 10 mL mark
- vigorously swish 10 milliliters of rinse between your teeth for 1 minute and then spit out
- do not swallow the rinse
- do not eat or drink for 30 minutes after rinsing
- instruct children under 12 years of age in good rinsing habits (to minimize swallowing)
- supervise children as necessary until capable of using without supervision

children under 6 years of age: consult a dentist or doctor

Other information

- contains FD&C yellow no. 5 (tartrazine) as a color additive
- do not use if safety seal is broken or missing

Inactive ingredients

water, sorbitol, poloxamer 407, propylene glycol, sodium phosphate, polysorbate 20, sodium saccharin, sucralose, disodium phosphate, cetylpyridinium chloride, calcium disodium EDTA, sodium benzoate, potassium sorbate, flavor, yellow 5, green 3 (309-166)

PRINCIPAL DISPLAY PANEL

ZERO ALCOHOL
ACT
1X Daily
RESTORING
ANTICAVITY FLUORIDE MOUTHWASH
MINT BURST
18 fl oz (532 mL)